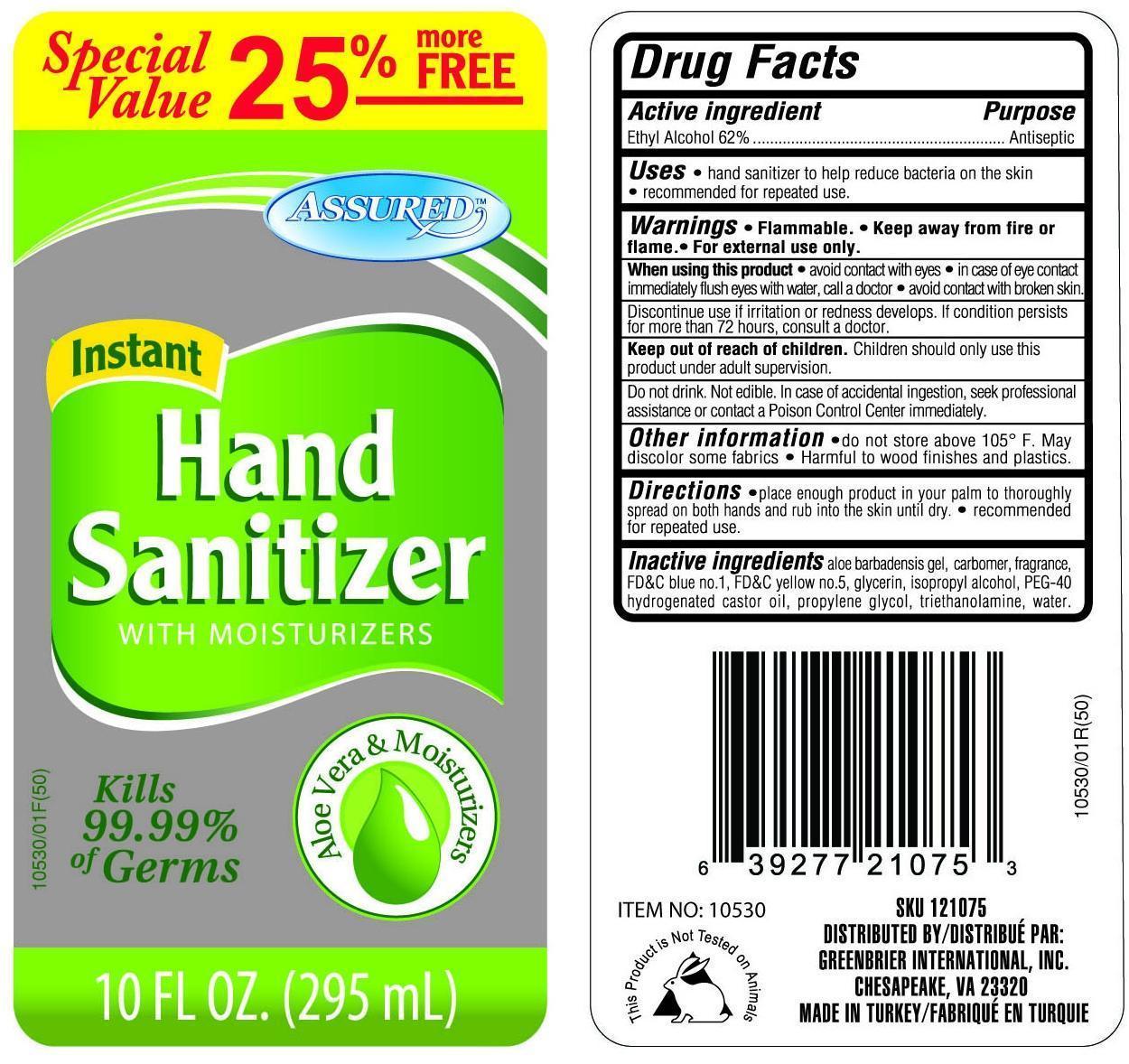 DRUG LABEL: Assured
NDC: 33992-4948 | Form: LIQUID
Manufacturer: Greenbrier International Inc.
Category: otc | Type: HUMAN OTC DRUG LABEL
Date: 20140613

ACTIVE INGREDIENTS: ALCOHOL 62 mL/100 mL
INACTIVE INGREDIENTS: ALOE; FD&C BLUE NO. 1; FD&C YELLOW NO. 5; GLYCERIN; ISOPROPYL ALCOHOL; POLYOXYL 40 HYDROGENATED CASTOR OIL; PROPYLENE GLYCOL; TROLAMINE; WATER

Drug Facts

Active Ingredient

Ethyl Alcohol 62%

Purpose
Antiseptic

INDICATIONS AND USAGE

Uses • hand sanitizer to help reduce bacteria on the skin •recommended for repeated use.

WARNINGS

Warnings •Flammable. • Keep away from fire and flame. •For external use only

When using this product •avoid contact with eyes • in case of eye contact immediately flush eyes with water, call a doctor • avoid contact with broken skin.
Discontinue use if irritation develops. If condition persists for more than 72 hours, consult a doctor.

Keep out of reach of children. Children should only use this product under adult supervision. Do not drink. Not edible. In case of accidental ingestion, seek professional assistance or contact a Poison Control Center immediately.

Other information • do not store above 105F. May discolor some fabrics. • Harmful to wood finishes and plastics

DOSAGE AND ADMINISTRATION

Directions • place enough product in your palm to thoroughly spread on both hands and rub into the skin until dry. • recommended for repeated use

INACTIVE INGREDIENT

Inactive ingredients aloe barbadensis gel, carbomer, fragrance, FD&C blue no. 1, FD&C yellow no.5, glycerin, isopropyl alcohol, PEG-40 hydrogenated castor oil, propylene glycol, triethanolamine, water